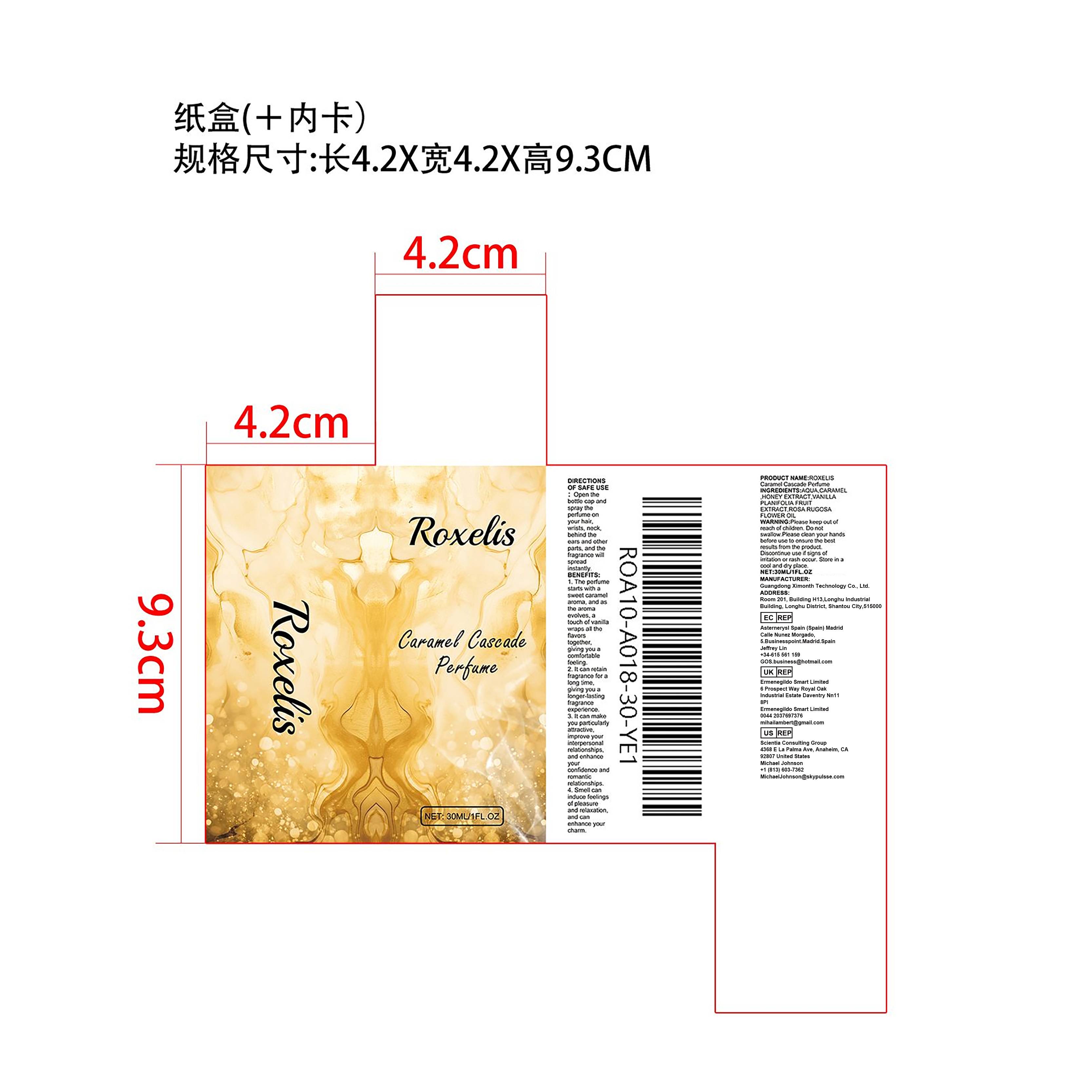 DRUG LABEL: CARAMEL CASCADE PERFUME
NDC: 84660-003 | Form: LIQUID
Manufacturer: Guangdong Ximonth Technology Co., Ltd.
Category: otc | Type: HUMAN OTC DRUG LABEL
Date: 20240822

ACTIVE INGREDIENTS: HONEY 3 mg/30 mg; VANILLA PLANIFOLIA FLOWER 9 mg/30 mg; ROSA RUGOSA FLOWER 18 mg/30 mg
INACTIVE INGREDIENTS: CARAMEL; WATER

Purpose

Perfume

Use

1. The perfume starts with a sweet caramel aroma, and as the aroma evolves, a touch of vanilla wraps all the flavors together, giving you a comfortable feeling.2. It can retain fragrance for a long time, giving you a longer-lasting fragrance experience.3. It can make you particularly attractive, improve your interpersonal relationships, and enhance your confidence and romantic relationships.4. Smell can induce feelings of pleasure and relaxation, and can enhance your charm.

Warnings

Please keep out of reach of children. Do not swallow.Please clean your hands before use to ensure the best results from the product. Discontinue use if signs of irritation or rash occur. Store in a cool and dry place.

STOP USE

Discontinue use if signs of irritation or rash occur.

Do not use

Discontinue use if signs of irritation or rash occur.

KEEP OUT OF REACH OF CHILDREN

Please keep out of reach of children. Do not swallow.

INACTIVE INGREDIENT

AQUA、CARAMEL

STORAGE AND HANDLING

Store in a cool and dry place.